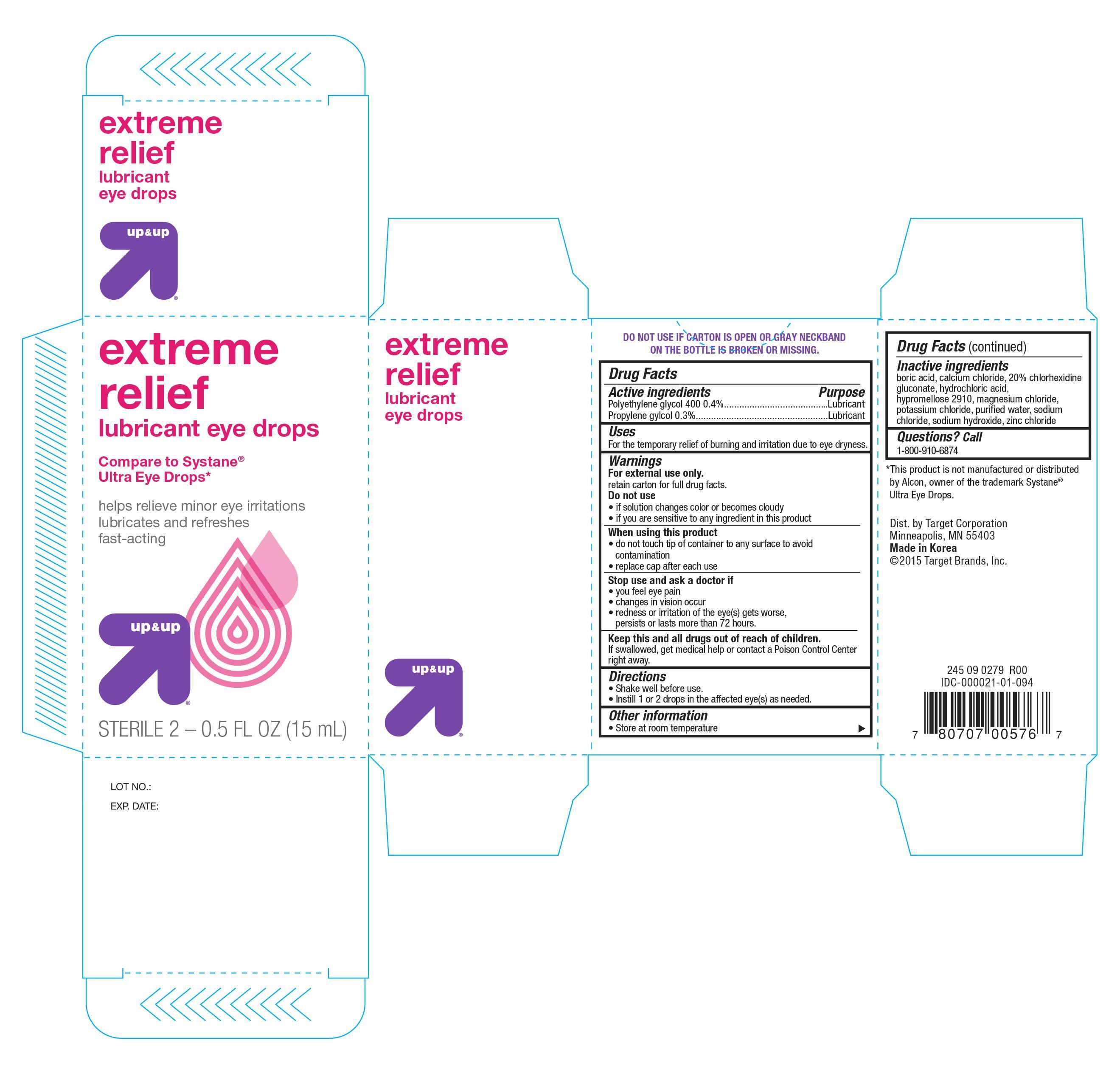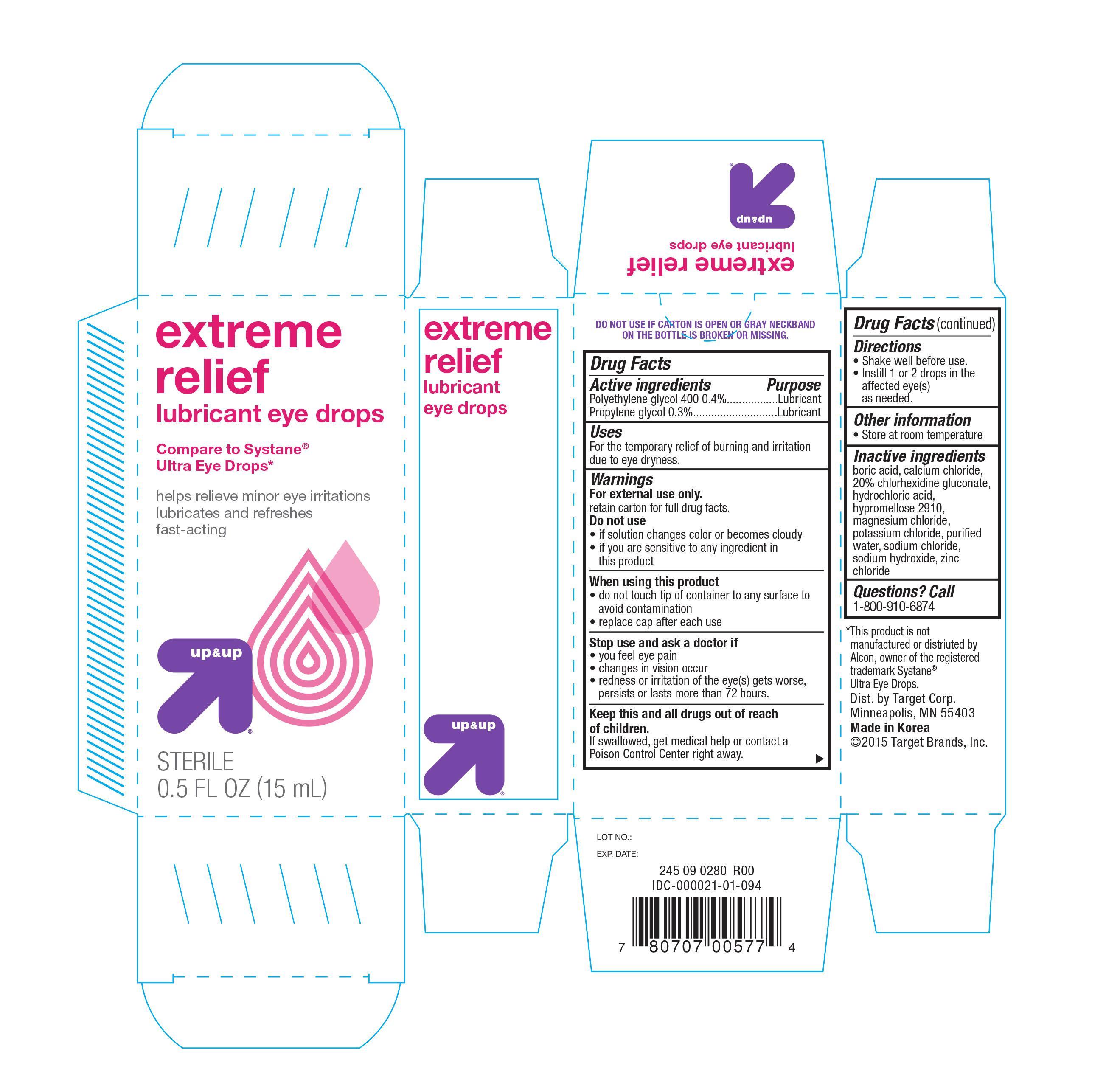 DRUG LABEL: Extreme Relief Lubricant
NDC: 11673-576 | Form: SOLUTION/ DROPS
Manufacturer: Target Corporation
Category: otc | Type: HUMAN OTC DRUG LABEL
Date: 20150304

ACTIVE INGREDIENTS: POLYETHYLENE GLYCOL 400 4 mg/1 mL; PROPYLENE GLYCOL 3 mg/1 mL
INACTIVE INGREDIENTS: BORIC ACID; CALCIUM CHLORIDE; CHLORHEXIDINE GLUCONATE; HYDROCHLORIC ACID; MAGNESIUM CHLORATE; POTASSIUM CHLORIDE; WATER; SODIUM CHLORIDE; SODIUM HYDROXIDE; ZINC CHLORIDE

Active ingredients Purpose

Polyethylene glycol 400 0.4%................................... Lubricant

Propylene glycol 0.3%............................................. Lubricant

Uses

For the temporary relief of burning and irritation due to eye dryness

Warnings

For external use only

retain carton for full drug facts

Do not use

- if solution changes color or becomes cloudy
- if you are sensitive to any ingredient in this product

When using this product

- do not touch tip of container to any surface to avoid contamination
- replace cap after each use

Stop use and ask a doctor if

- you feel eye pain
- changes in vision occur
- redness or irritation of the eye(s) gets worse, persists or last more than 72 hours

KEEP OUT OF REACH OF CHILDREN

Keep this and all drugs out of reach of children. If swallowed, get medical help or contact a Poison Control Center right away

Directions

- Shake well before use
- Instill 1 or 2 drops in the affected eye(s) as needed

Other information

- Store at room temperature

Inactive ingredients

boric acid, calcium chloride, 20% chlorhexidine, glyconate, hydrochloric acid, hypromellose 2910, magnesium chloride, potassium chloride, purified water, sodium chloride, sodium hydroxide, zinc chloride

DOSAGE AND ADMINISTRATION

DISTRIBUTED BY:

TARGET CORP.

MINNEAPOLIS, MN 55403

MADE IN KOREA